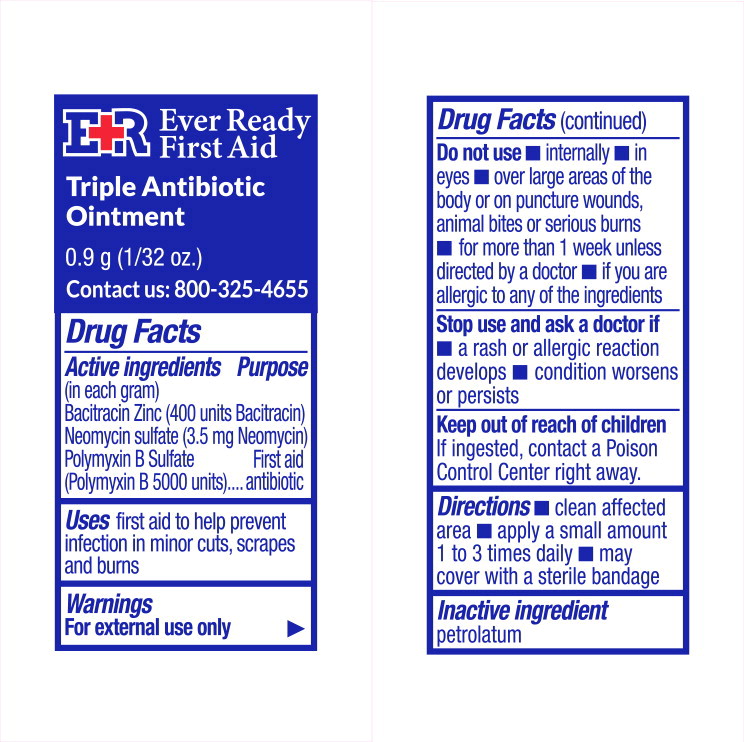 DRUG LABEL: Ever Ready Triple Antibiotic
NDC: 72976-563 | Form: OINTMENT
Manufacturer: Ever Ready
Category: otc | Type: HUMAN OTC DRUG LABEL
Date: 20230116

ACTIVE INGREDIENTS: bacitracin zinc 400 [USP'U]/1 g; neomycin sulfate 3.5 mg/1 g; polymyxin b sulfate 5000 [USP'U]/1 g
INACTIVE INGREDIENTS: WHITE PETROLATUM

Drug Facts

Active ingredients

(in each gram)

Bacitracin Zinc (400 units Bacitracin)

Neomycin sulfate (3.5 mg Neomycin)

Polymyxin B Sulfate (Polymyxin B 5000 units)

Purpose

First aid antibiotic

Uses

first aid to help prevent infection in minor cuts, scrapes and burns

Warnings

For external use only

Do not use

- internally
- in eyes
- over large areas of the body or on puncture wounds, animal bites or serious burns
- for more than 1 week unless directed by a doctor
- if you are allergic to any of the ingredients

Stop use and ask a doctor if

- a rash or allergic reaction develops
- condition worsens or persists

Keep out of reach of children

If ingested, contact a Poison Control Center right away.

Directions

- clean affected area
- apply a small amount 1 to 3 times daily
- may cover with a sterile bandage

Inactive ingredient

petrolatum

Principal Display Panel - 0.9g Pouch Label

E+R Ever Ready
First Aid

Triple Antibiotic
Ointment

0.9 g (1/32 oz.)

Contact us: 800-325-4655